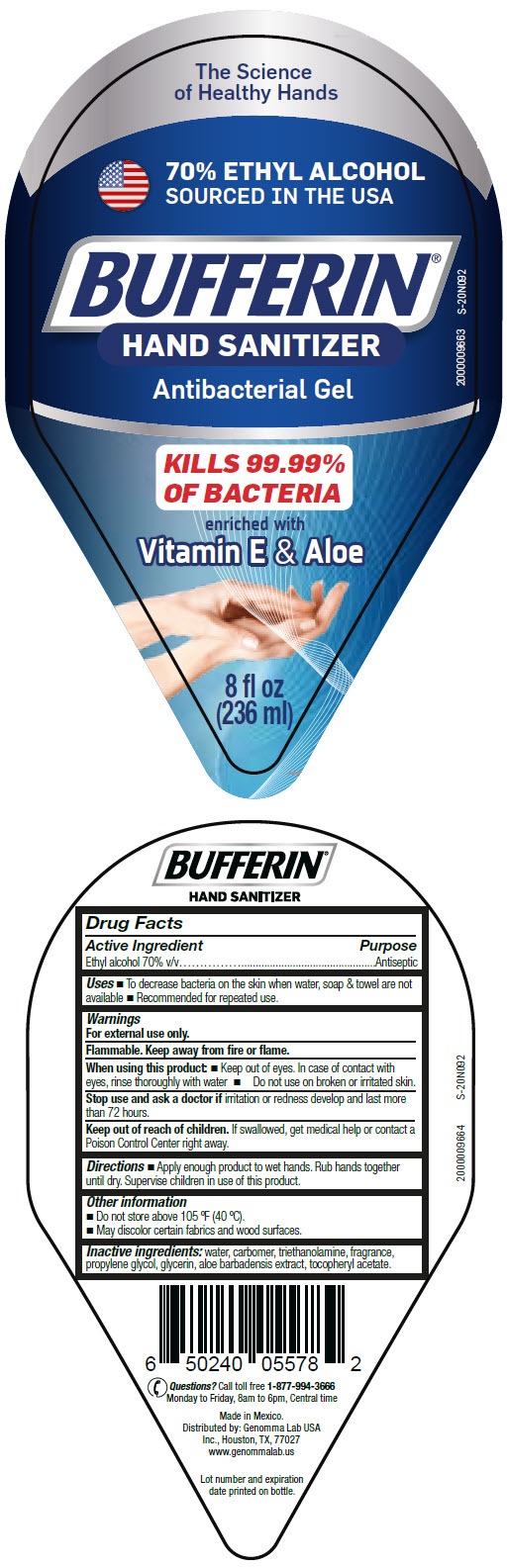 DRUG LABEL: Bufferin Hand Sanitizer
NDC: 50066-608 | Form: GEL
Manufacturer: Genomma Lab USA
Category: otc | Type: HUMAN OTC DRUG LABEL
Date: 20200915

ACTIVE INGREDIENTS: ALCOHOL 70 mL/100 mL
INACTIVE INGREDIENTS: Glycerin; Water; CARBOMER HOMOPOLYMER, UNSPECIFIED TYPE; TROLAMINE; Propylene glycol

Bufferin® Hand Sanitizer

Drug Facts

Active Ingredient

Ethyl alcohol 70% v/v

Purpose

Antiseptic

Uses

- To decrease bacteria on the skin when water, soap & towel are not available
- Recommended for repeated use.

Warnings

For external use only.

Flammable. Keep away from fire or flame.

When using this product

- Keep out of eyes. In case of contact with eyes, rinse thoroughly with water
- Do not use on broken or irritated skin.

Stop use and ask a doctor if irritation or redness develop and last more than 72 hours.

Keep out of reach of children. If swallowed, get medical help or contact a Poison Control Center right away.

Directions

- Apply enough product to wet hands. Rub hands together until dry. Supervise children in use of this product.

Other information

- Do not store above 105 °F (40 °C).
- May discolor certain fabrics and wood surfaces.

Inactive ingredients

water, carbomer, triethanolamine, fragrance, propylene glycol, glycerin, aloe barbadensis extract, tocopheryl acetate.

Questions?

Call toll free 1-877-994-3666 Monday to Friday, 8am to 6pm, Central time

Distributed by: Genomma Lab USA
Inc., Houston, TX, 77027

PRINCIPAL DISPLAY PANEL - 236 ml Bottle Label

The Science
of Healthy Hands

70% ETHYL ALCOHOL
SOURCED IN THE USA

BUFFERIN®
HAND SANITIZER

Antibacterial Gel

KILLS 99.99%
OF BACTERIA

enriched with
Vitamin E & Aloe

8 fl oz
(236 ml)

2000009663
S-20N092